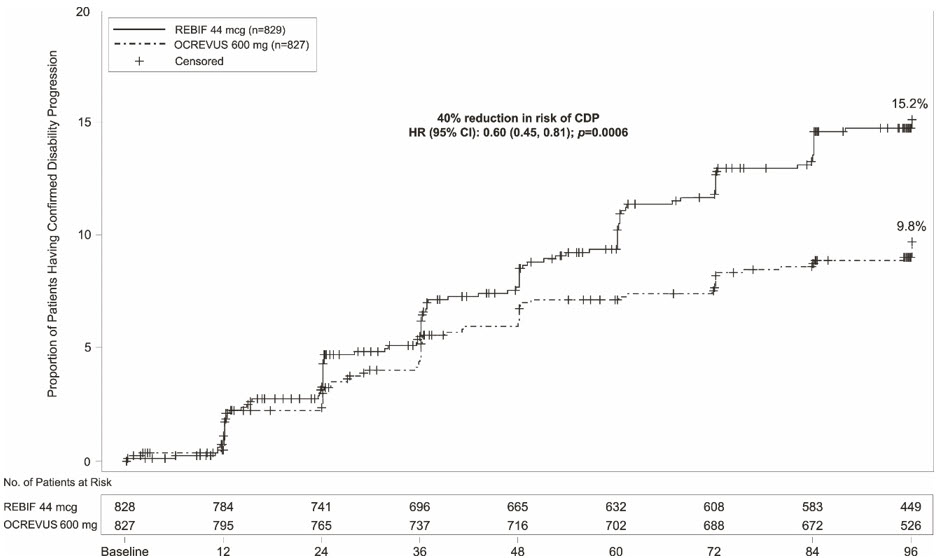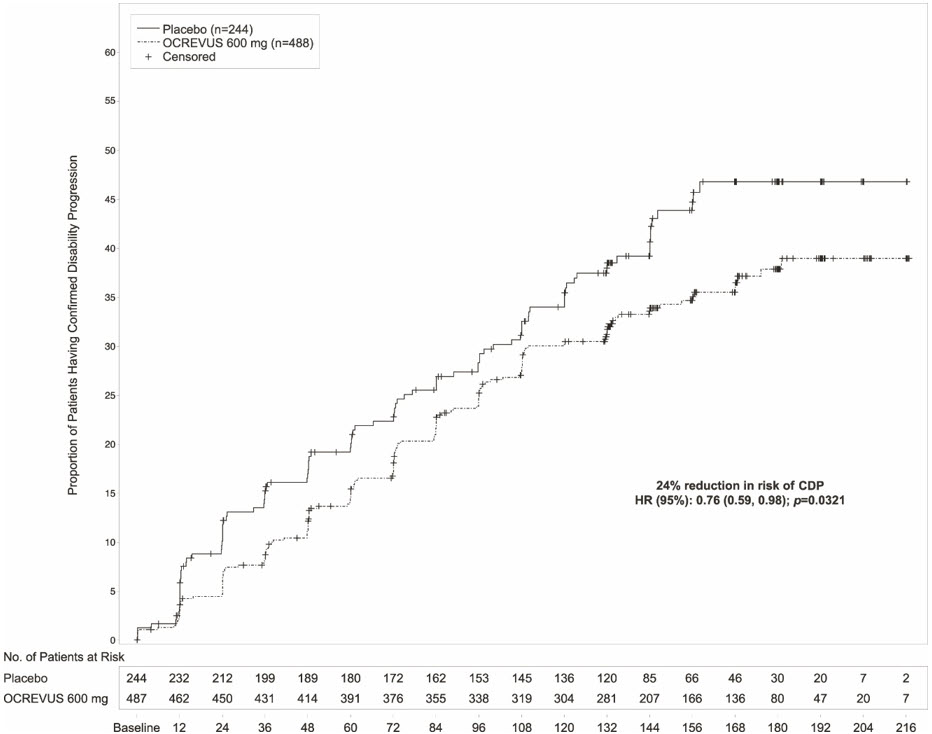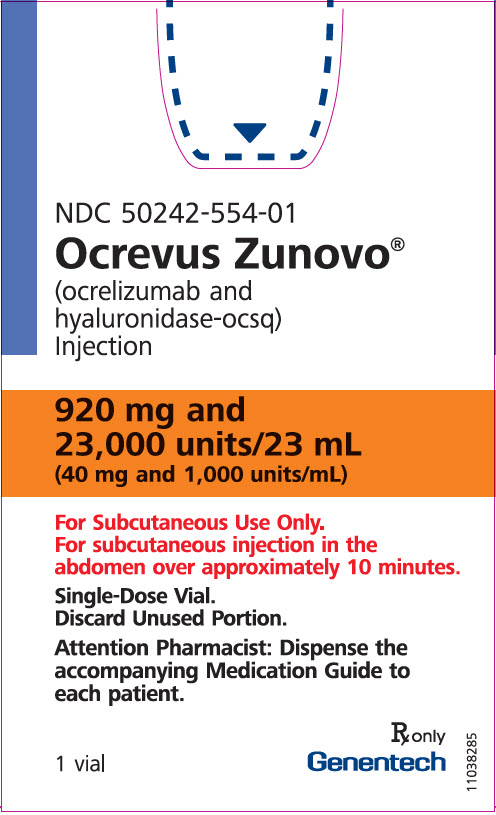 DRUG LABEL: Ocrevus Zunovo
NDC: 50242-554 | Form: INJECTION, SOLUTION
Manufacturer: Genentech, Inc.
Category: prescription | Type: HUMAN PRESCRIPTION DRUG LABEL
Date: 20251211

ACTIVE INGREDIENTS: OCRELIZUMAB 920 mg/23 mL; HYALURONIDASE (HUMAN RECOMBINANT) 23000 U/23 mL
INACTIVE INGREDIENTS: TREHALOSE DIHYDRATE 1889.5 mg/23 mL; ACETIC ACID 5.5 mg/23 mL; METHIONINE 34.3 mg/23 mL; POLYSORBATE 20 13.8 mg/23 mL; SODIUM ACETATE 30.2 mg/23 mL; WATER

HIGHLIGHTS OF PRESCRIBING INFORMATION

These highlights do not include all the information needed to use OCREVUS ZUNOVO safely and effectively. See full prescribing information for OCREVUS ZUNOVO.
OCREVUS ZUNOVO® (ocrelizumab and hyaluronidase-ocsq) injection, for subcutaneous use
Initial U.S. Approval: 2024

RECENT MAJOR CHANGES

Dosage and Administration (2.2) | 8/2025
Warnings and Precautions (5.7) | 8/2025

1 INDICATIONS AND USAGE

OCREVUS ZUNOVO is a CD20-directed cytolytic antibody indicated for the treatment of:

- Relapsing forms of multiple sclerosis (MS), to include clinically isolated syndrome, relapsing-remitting disease, and active secondary progressive disease, in adults (1)
- Primary progressive MS, in adults (1)

2 DOSAGE AND ADMINISTRATION

- OCREVUS ZUNOVO should be administered by a healthcare professional (2.1)
- For subcutaneous use in the abdomen only (2.1)
- OCREVUS ZUNOVO has different dosage and administration instructions than intravenous ocrelizumab (2.1)
- Before initiating OCREVUS ZUNOVO, screen for Hepatitis B virus and obtain serum quantitative immunoglobulins, aminotransferases, alkaline phosphatase, and bilirubin (2.2)
- Pre-medicate orally with dexamethasone (or an equivalent corticosteroid) and an antihistamine (e.g., desloratadine) at least 30 minutes prior to each injection (2.3)
- Administer 23 mL of OCREVUS ZUNOVO (920 mg ocrelizumab and 23,000 units hyaluronidase) subcutaneously in the abdomen over approximately 10 minutes every 6 months (2.4)
- Monitor patients closely during all injections, for at least one hour after the initial injection, and for at least 15 minutes after subsequent injections (2.4)

3 DOSAGE FORMS AND STRENGTHS

- Injection: 920 mg ocrelizumab and 23,000 units hyaluronidase per 23 mL (40 mg and 1,000 units per mL) solution in a single-dose vial (3)

4 CONTRAINDICATIONS

- Active hepatitis B virus infection (4)
- History of life-threatening administration reactions to ocrelizumab (4)
- History of hypersensitivity to ocrelizumab, hyaluronidase, or to any component of OCREVUS ZUNOVO (4)

5 WARNINGS AND PRECAUTIONS

- Injection Reactions: Management recommendations for injection reactions depend on the type and severity of the reaction. Permanently discontinue OCREVUS ZUNOVO if a life-threatening injection reaction occurs (4, 5.1)
- Infections: Serious, including life-threatening and fatal, infections have occurred in patients treated with ocrelizumab. Delay OCREVUS ZUNOVO administration in patients with an active infection until the infection is resolved. Vaccination with live-attenuated or live vaccines is not recommended during treatment with OCREVUS ZUNOVO and after discontinuation, until B-cell repletion (5.2)
- Progressive Multifocal Leukoencephalopathy (PML): Withhold OCREVUS ZUNOVO at the first sign or symptom suggestive of PML (5.3)
- Reduction in Immunoglobulins: Monitor the level of immunoglobulins at the beginning of treatment. Monitor during and after discontinuation of treatment with OCREVUS ZUNOVO, until B-cell repletion, and especially when recurrent serious infections are suspected. Consider discontinuing OCREVUS ZUNOVO in patients with serious opportunistic or recurrent serious infections, and if prolonged hypogammaglobulinemia requires treatment with intravenous immunoglobulins (2.1, 5.4)
- Malignancies: An increased risk of malignancy, including breast cancer, may exist with OCREVUS ZUNOVO (5.5)
- Immune-Mediated Colitis: Immune-mediated colitis has been reported in the postmarketing setting. Monitor patients for new or persistent diarrhea or other gastrointestinal symptoms, and evaluate promptly if colitis is suspected (5.6)
- Liver Injury: Clinically significant liver injury has occurred. Obtain serum aminotransferases, alkaline phosphatase, and bilirubin levels before initiating OCREVUS ZUNOVO, and during treatment as clinically indicated. Discontinue OCREVUS ZUNOVO in patients with evidence of liver injury in the absence of an alternative etiology (5.7)

6 ADVERSE REACTIONS

The most common adverse reactions in patients treated with intravenous ocrelizumab were:

- RMS (incidence ≥10% and > REBIF®): upper respiratory tract infections and infusion reactions (6.1)
- PPMS (incidence ≥10% and > placebo): upper respiratory tract infections, infusion reactions, skin infections, and lower respiratory tract infections (6.1)

The most common adverse reaction observed with OCREVUS ZUNOVO in patients with RMS and PPMS was injection reactions (incidence of 49%) (6.1)

To report SUSPECTED ADVERSE REACTIONS, contact Genentech at 1-888-835-2555 or FDA at 1-800-FDA-1088 or www.fda.gov/medwatch.

8 USE IN SPECIFIC POPULATIONS

- Pregnancy: Based on animal data, may cause fetal harm (8.1)

FULL PRESCRIBING INFORMATION

1 INDICATIONS AND USAGE

OCREVUS ZUNOVO is indicated for the treatment of:

- Relapsing forms of multiple sclerosis (MS), to include clinically isolated syndrome, relapsing-remitting disease, and active secondary progressive disease, in adults
- Primary progressive MS, in adults

2 DOSAGE AND ADMINISTRATION

2.1 Important Administration Information

OCREVUS ZUNOVO is for subcutaneous use in the abdomen only.

OCREVUS ZUNOVO has different dosage and administration instructions than intravenous ocrelizumab.

OCREVUS ZUNOVO should be administered via subcutaneous injection by a healthcare professional.

2.2 Assessments Prior to First Dose of OCREVUS ZUNOVO

Hepatitis B Virus Screening

Prior to initiating ocrelizumab treatment, perform Hepatitis B virus (HBV) screening. OCREVUS ZUNOVO is contraindicated in patients with active HBV confirmed by positive results for HBsAg and anti-HBV tests. For patients who are negative for surface antigen [HBsAg] and positive for HB core antibody [HBcAb+] or are carriers of HBV [HBsAg+], consult liver disease experts before starting and during treatment [see Warnings and Precautions (5.2)].

Serum Immunoglobulins

Prior to initiating ocrelizumab treatment, perform testing for quantitative serum immunoglobulins [see Warnings and Precautions (5.4)]. For patients with low serum immunoglobulins, consult immunology experts before initiating treatment with ocrelizumab.

Vaccinations

Because vaccination with live-attenuated or live vaccines is not recommended during treatment and after discontinuation until B-cell repletion, administer all immunizations according to immunization guidelines at least 4 weeks prior to initiation of ocrelizumab treatment for live or live-attenuated vaccines and, whenever possible, at least 2 weeks prior to initiation of ocrelizumab treatment for non-live vaccines [see Warnings and Precautions (5.2) and Clinical Pharmacology (12.2)].

Liver Function Tests

Prior to initiating OCREVUS ZUNOVO, obtain serum aminotransferases (alanine aminotransferase [ALT] and aspartate aminotransferase [AST]), alkaline phosphatase, and bilirubin levels [see Warnings and Precautions (5.7)].

2.3 Assessments and Premedication Prior to Every Dose

Infection Assessment

Prior to every dose of OCREVUS ZUNOVO, determine whether there is an active infection. In case of active infection, delay administration of OCREVUS ZUNOVO until the infection resolves [see Warnings and Precautions (5.2)].

Recommended Premedication

Pre-medicate orally with 20 mg of dexamethasone (or an equivalent corticosteroid) and an antihistamine (e.g., desloratadine) administered at least 30 minutes prior to each OCREVUS ZUNOVO administration to reduce the risk of local and systemic injection reactions [see Warnings and Precautions (5.1)].

The addition of an antipyretic (e.g., acetaminophen) may also be considered.

2.4 Recommended Dosage

The recommended dosage of OCREVUS ZUNOVO is 920 mg/23,000 units (920 mg ocrelizumab and 23,000 units of hyaluronidase) administered as a single 23 mL subcutaneous injection in the abdomen over approximately 10 minutes every 6 months.

Monitor the patient closely during injections, with access to appropriate medical support to manage severe injection reactions. For the initial dose, monitor the patient for at least one hour post-injection. For subsequent doses, monitor the patient for at least 15 minutes post-injection [see Warnings and Precautions (5.1)].

2.5 Delayed or Missed Doses

If a planned injection of OCREVUS ZUNOVO is missed, administer OCREVUS ZUNOVO as soon as possible; do not wait until the next scheduled dose. Reset the dose schedule to administer the next sequential dose 6 months after the missed dose is administered. Doses of OCREVUS ZUNOVO must be separated by at least 5 months [see Dosage and Administration (2.4)].

2.6 Preparation and Administration

To prevent medication errors, check the vial labels to ensure that the drug being prepared and administered is OCREVUS ZUNOVO and not intravenous ocrelizumab.

Visually inspect the vial for particulate matter and discoloration prior to administration, whenever solution and container permit. Do not use the vial if particulates or discoloration are present. Do not shake. Discard any unused portion remaining in the vial.

OCREVUS ZUNOVO is compatible with polypropylene (PP), polycarbonate (PC), polyethylene (PE), stainless steel (SS), polyvinylchloride (PVC), and polyurethane (PUR).

Preparation of the Syringe

OCREVUS ZUNOVO should be prepared by a healthcare professional.

- Immediate use is recommended, as OCREVUS ZUNOVO does not contain any antimicrobial preservative. If the dose is not administered immediately, refer to "Storage of the Syringe" below.
- Remove the vial from refrigerated storage and allow the solution to acclimate to room temperature at or below 25°C (77°F).
- Withdraw the entire contents of OCREVUS ZUNOVO solution from the vial with a syringe and transfer needle (21G needle recommended).
- Do not dilute.
- Remove the transfer needle from the syringe and replace with a subcutaneous infusion set (e.g., winged/butterfly) containing a 24G-26G needle for injection. Use a subcutaneous infusion set with a priming volume NOT to exceed 0.8 mL for administration.
- Prime the subcutaneous infusion line with the drug product solution to eliminate the air in the infusion line and stop before the fluid reaches the needle.
- Ensure the syringe contains exactly 23 mL of drug product solution after priming and expelling any excess volume from the syringe.
- Administer immediately to avoid needle clogging. DO NOT store the prepared syringe that has been attached to the already primed subcutaneous infusion set.

Administration

- Administer 23 mL of OCREVUS ZUNOVO subcutaneously in the abdomen over approximately 10 minutes. DO NOT administer the remaining priming volume in the subcutaneous infusion set to the patient.
- The recommended injection site is the abdomen, except for 2 inches (5 cm) around the navel. Do not administer OCREVUS ZUNOVO injections into areas where the skin is red, bruised, tender, or hard, or areas where there are moles or scars.

Storage of the Syringe

- If the dose is not to be administered immediately, use aseptic technique to withdraw the entire OCREVUS ZUNOVO contents from the vial into the syringe to account for the dose volume (23 mL) plus the priming volume for the subcutaneous infusion set. Replace the transfer needle with a syringe closing cap. DO NOT attach a subcutaneous infusion set.
- If not used immediately, the closed syringe can be refrigerated (2°C to 8°C [36°F to 46°F]) for up to 72 hours followed by 8 hours at ambient temperatures at or below 25°C (77°F) in diffuse daylight.
- If the prepared syringe was stored at 2°C to 8°C (36°F to 46°F), allow the syringe to acclimate to room temperature prior to administration.

3 DOSAGE FORMS AND STRENGTHS

Injection: 920 mg ocrelizumab and 23,000 units hyaluronidase per 23 mL (40 mg and 1,000 units per mL) clear to slightly opalescent, and colorless to pale brown solution in a single-dose vial.

4 CONTRAINDICATIONS

OCREVUS ZUNOVO is contraindicated in patients with:

- Active HBV infection [see Dosage and Administration (2.2) and Warnings and Precautions (5.2)]
- A history of life-threatening administration reaction to ocrelizumab [see Warnings and Precautions (5.1)]
- A history of hypersensitivity to ocrelizumab, hyaluronidase, or any component of OCREVUS ZUNOVO [see Warnings and Precautions (5.1)].

5 WARNINGS AND PRECAUTIONS

5.1 Injection Reactions

OCREVUS ZUNOVO can cause injection reactions, which can be local or systemic. Common symptoms of local injection reactions reported by patients treated with OCREVUS ZUNOVO in multiple sclerosis (MS) clinical trials included erythema, pain, swelling, and pruritus. Common symptoms of systemic injection reactions reported by patients included headache and nausea. In an open-label, active-controlled trial, injection reactions were more frequently reported with the first injection; 49% of patients experienced an injection reaction with the first injection [see Adverse Reactions (6.1)].

In MS clinical trials where ocrelizumab was administered intravenously, the incidence of infusion reactions in patients [who received methylprednisolone (or an equivalent steroid) and possibly other premedication to reduce the risk of infusion reactions prior to infusion] was 34% to 40%, with the highest incidence with the first infusion. There were no fatal infusion reactions, but 0.3% of intravenous ocrelizumab-treated MS patients experienced infusion reactions that were serious, some requiring hospitalization. Symptoms of infusion reactions can include pruritus, rash, urticaria, erythema, bronchospasm, throat irritation, oropharyngeal pain, dyspnea, pharyngeal or laryngeal edema, flushing, hypotension, pyrexia, fatigue, headache, dizziness, nausea, tachycardia, and anaphylaxis.

Monitor patients during and after injections [see Dosage and Administration (2.4)]. Inform patients that injection reactions can occur during or within 24 hours of the injection.

Reducing the Risk of Injection Reactions and Managing Injection Reactions

Administer oral premedication (e.g., dexamethasone or an equivalent corticosteroid, and an antihistamine) at least 30 minutes prior to each OCREVUS ZUNOVO injection to reduce the risk of injection reactions. The addition of an antipyretic (e.g., acetaminophen) may also be considered [see Dosage and Administration (2.3)].

Management recommendations for injection reactions depend on the type and severity of the reaction. For life-threatening injection reactions, immediately and permanently stop OCREVUS ZUNOVO and administer appropriate supportive treatment. For less severe injection reactions, the injection should be interrupted immediately, and the patient should receive symptomatic treatment. The injection should be completed at the healthcare provider's discretion and only after all symptoms have resolved.

5.2 Infections

Serious, including life-threatening or fatal, bacterial, viral, parasitic, and fungal infections have been reported in patients receiving ocrelizumab. An increased risk of infections (including serious and fatal bacterial, fungal, and new or reactivated viral infections) has been observed in patients during and following completion of treatment with anti-CD20 B-cell depleting therapies.

A higher proportion of intravenous ocrelizumab-treated patients experienced infections compared to patients taking REBIF or placebo. In RMS trials, 58% of intravenous ocrelizumab-treated patients experienced one or more infections compared to 52% of REBIF-treated patients. In the PPMS trial, 70% of intravenous ocrelizumab-treated patients experienced one or more infections compared to 68% of patients on placebo.

Intravenous ocrelizumab was not associated with an increased risk of serious infections in MS patients in controlled trials.

Ocrelizumab increases the risk for upper respiratory tract infections, lower respiratory tract infections, skin infections, and herpes-related infections [see Adverse Reactions (6.1)].

Delay OCREVUS ZUNOVO administration in patients with an active infection until the infection is resolved.

Respiratory Tract Infections

A higher proportion of intravenous ocrelizumab-treated patients experienced respiratory tract infections compared to patients taking REBIF or placebo. In RMS trials, 40% of patients treated with intravenous ocrelizumab experienced upper respiratory tract infections compared to 33% of REBIF-treated patients, and 8% of patients treated with intravenous ocrelizumab experienced lower respiratory tract infections compared to 5% of REBIF-treated patients. In the PPMS trial, 49% of patients treated with intravenous ocrelizumab experienced upper respiratory tract infections compared to 43% of patients on placebo, and 10% of patients treated with intravenous ocrelizumab experienced lower respiratory tract infections compared to 9% of patients on placebo. The infections were predominantly mild to moderate and consisted mostly of upper respiratory tract infections and bronchitis.

Herpes

In active-controlled (RMS) clinical trials, herpes infections were reported more frequently in patients treated with intravenous ocrelizumab than in REBIF-treated patients, including herpes zoster (2.1% vs. 1.0%), herpes simplex (0.7% vs. 0.1%), oral herpes (3.0% vs. 2.2%), genital herpes (0.1% vs. 0%), and herpes virus infection (0.1% vs. 0%). Infections were predominantly mild to moderate in severity.

In the placebo-controlled (PPMS) clinical trial, oral herpes was reported more frequently in the patients treated with intravenous ocrelizumab than in the patients on placebo (2.7% vs. 0.8%).

Serious cases of infections caused by herpes simplex virus and varicella zoster virus, including central nervous system infections (encephalitis and meningitis), intraocular infections, and disseminated skin and soft tissue infections, have been reported in the postmarketing setting in multiple sclerosis patients receiving ocrelizumab. Some cases were life-threatening. Serious herpes virus infections may occur at any time during treatment with OCREVUS ZUNOVO.

If serious herpes infections occur, OCREVUS ZUNOVO should be discontinued or withheld until the infection has resolved, and appropriate treatment should be administered [see Patient Counseling Information (17)].

Hepatitis B Virus Reactivation

Hepatitis B virus (HBV) reactivation has been reported in MS patients treated with ocrelizumab in the postmarketing setting. Fulminant hepatitis, hepatic failure, and death caused by HBV reactivation have occurred in patients treated with anti-CD20 antibodies. Perform HBV screening in all patients before initiation of treatment with ocrelizumab. Do not administer OCREVUS ZUNOVO to patients with active HBV confirmed by positive results for HBsAg and anti-HB tests. For patients who are negative for surface antigen [HBsAg] and positive for HB core antibody [HBcAb+] or are carriers of HBV [HBsAg+], consult liver disease experts before starting and during treatment.

Possible Increased Risk of Immunosuppressant Effects With Other Immunosuppressants

When initiating OCREVUS ZUNOVO after an immunosuppressive therapy or initiating an immunosuppressive therapy after OCREVUS ZUNOVO, consider the potential for increased immunosuppressive effects [see Drug Interactions (7.1) and Clinical Pharmacology (12.1, 12.2)]. OCREVUS ZUNOVO has not been studied in combination with other MS therapies.

Vaccinations

Administer all immunizations according to immunization guidelines at least 4 weeks prior to initiation of ocrelizumab treatment for live or live-attenuated vaccines and, whenever possible, at least 2 weeks prior to initiation of ocrelizumab for non-live vaccines.

OCREVUS ZUNOVO may interfere with the effectiveness of non-live vaccines [see Drug Interactions (7.2)].

The safety of immunization with live or live-attenuated vaccines following OCREVUS ZUNOVO therapy has not been studied, and vaccination with live-attenuated or live vaccines is not recommended during treatment and until B-cell repletion [see Clinical Pharmacology (12.2)].

Vaccination of Infants Born to Mothers Treated with OCREVUS ZUNOVO During Pregnancy

In infants of mothers exposed to OCREVUS ZUNOVO during pregnancy, do not administer live or live-attenuated vaccines before confirming the recovery of B-cell counts as measured by CD19^+ B-cells. Depletion of B-cells in these infants may increase the risks from live or live-attenuated vaccines.

You may administer non-live vaccines, as indicated, prior to recovery from B-cell depletion, but should consider assessing vaccine immune responses, including consultation with a qualified specialist, to assess whether a protective immune response was mounted [see Use in Specific Populations (8.1)].

5.3 Progressive Multifocal Leukoencephalopathy

Cases of progressive multifocal leukoencephalopathy (PML) have been reported in patients with MS treated with ocrelizumab in the postmarketing setting. PML is an opportunistic viral infection of the brain caused by the JC virus (JCV) that typically only occurs in patients who are immunocompromised, and that usually leads to death or severe disability. PML has occurred in ocrelizumab-treated patients who had not been treated previously with natalizumab (which has a known association with PML), were not taking any immunosuppressive or immunomodulatory medications associated with the risk of PML prior to or concomitantly with ocrelizumab, and did not have any known ongoing systemic medical conditions resulting in compromised immune system function.

JCV infection resulting in PML has also been observed in patients treated with other anti-CD20 antibodies and other MS therapies.

At the first sign or symptom suggestive of PML, withhold OCREVUS ZUNOVO and perform an appropriate diagnostic evaluation. Typical symptoms associated with PML are diverse, progress over days to weeks, and include progressive weakness on one side of the body or clumsiness of limbs, disturbance of vision, and changes in thinking, memory, and orientation leading to confusion and personality changes.

MRI findings may be apparent before clinical signs or symptoms. Cases of PML, diagnosed based on MRI findings and the detection of JCV DNA in the cerebrospinal fluid in the absence of clinical signs or symptoms specific to PML, have been reported in patients treated with other MS medications associated with PML. Many of these patients subsequently became symptomatic with PML. Therefore, monitoring with MRI for signs that may be consistent with PML may be useful, and any suspicious findings should lead to further investigation to allow for an early diagnosis of PML, if present. Following discontinuation of another MS medication associated with PML, lower PML-related mortality and morbidity have been reported in patients who were initially asymptomatic at diagnosis compared to patients who had characteristic clinical signs and symptoms at diagnosis.

It is not known whether these differences are due to early detection and discontinuation of MS treatment or due to differences in disease in these patients.

If PML is confirmed, treatment with OCREVUS ZUNOVO should be discontinued.

5.4 Reduction in Immunoglobulins

As expected with any B-cell depleting therapy, decreased immunoglobulin levels are observed with ocrelizumab treatment. The pooled data of intravenous ocrelizumab clinical studies (RMS and PPMS) and their open-label extensions (up to approximately 7 years of exposure) have shown an association between decreased levels of immunoglobulin G (IgG<LLN) and increased rates of serious infections. Monitor the levels of quantitative serum immunoglobulins during OCREVUS ZUNOVO treatment and after discontinuation of treatment, until B-cell repletion, and especially in the setting of recurrent serious infections. Consider discontinuing OCREVUS ZUNOVO therapy in patients with serious opportunistic or recurrent serious infections, and if prolonged hypogammaglobulinemia requires treatment with intravenous immunoglobulins [see Adverse Reactions (6.1)].

5.5 Malignancies

An increased risk of malignancy with OCREVUS ZUNOVO may exist. In controlled trials, malignancies, including breast cancer, occurred more frequently in patients treated with intravenous ocrelizumab. Breast cancer occurred in 6 of 781 females treated with intravenous ocrelizumab and none of 668 females treated with REBIF or placebo. Patients should follow standard breast cancer screening guidelines.

5.6 Immune-Mediated Colitis

Immune-mediated colitis, which can present as a severe and acute-onset form of colitis, has been reported in patients receiving ocrelizumab in the postmarketing setting. Some cases of colitis were serious, requiring hospitalization, with a few patients requiring surgical intervention. Systemic corticosteroids were required in many of these patients. The time from treatment initiation to onset of symptoms in these cases ranged from a few weeks to years. Monitor patients for immune-mediated colitis during OCREVUS ZUNOVO treatment, and evaluate promptly if signs and symptoms that may indicate immune-mediated colitis, such as new or persistent diarrhea or other gastrointestinal signs and symptoms, occur.

5.7 Liver Injury

Clinically significant liver injury, without findings of viral hepatitis, has been reported in the postmarketing setting in patients treated with anti-CD20 B-cell depleting therapies approved for the treatment of MS, including ocrelizumab. Signs of liver injury, including markedly elevated serum hepatic enzymes with elevated total bilirubin, have occurred from weeks to months after administration.

Patients treated with OCREVUS ZUNOVO found to have an alanine aminotransferase (ALT) or aspartate aminotransferase (AST) greater than 3× the upper limit of normal (ULN) with serum total bilirubin greater than 2× ULN are potentially at risk for severe drug-induced liver injury.

Obtain liver function tests prior to initiating treatment with OCREVUS ZUNOVO [see Dosage and Administration (2.2)], and monitor for signs and symptoms of any hepatic injury during treatment. Measure serum aminotransferases, alkaline phosphatase, and bilirubin levels promptly in patients who report symptoms that may indicate liver injury, including new or worsening fatigue, anorexia, nausea, vomiting, right upper abdominal discomfort, dark urine, or jaundice. If liver injury is present and an alternative etiology is not identified, discontinue OCREVUS ZUNOVO.

6 ADVERSE REACTIONS

The following serious adverse reactions are discussed in greater detail in other sections of the labeling:

- Injection Reactions [see Warnings and Precautions (5.1)]
- Infections [see Warnings and Precautions (5.2)]
- Progressive Multifocal Leukoencephalopathy [see Warnings and Precautions (5.3)]
- Reduction in Immunoglobulins [see Warnings and Precautions (5.4)]
- Malignancies [see Warnings and Precautions (5.5)]
- Immune-Mediated Colitis [see Warnings and Precautions (5.6)]
- Liver Injury [see Warnings and Precautions (5.7)]

6.1 Clinical Trials Experience

Because clinical trials are conducted under widely varying conditions, adverse reaction rates observed in the clinical trials of a drug cannot be directly compared to rates in the clinical trials of another drug and may not reflect the rates observed in clinical practice.

The safety of ocrelizumab has been evaluated in active-controlled clinical trials of ocrelizumab administered intravenously in patients with relapsing forms of MS (RMS) (Study 1 and Study 2) [see Clinical Studies (14.1)] and primary progressive MS (PPMS) (Study 3) [see Clinical Studies (14.2)], and in an open-label, active-controlled trial of OCREVUS ZUNOVO administered subcutaneously in patients with RMS and PPMS (Study 4) [see Clinical Studies (14.3)].

Adverse Reactions With Ocrelizumab Intravenous in Patients With RMS and PPMS

The safety of intravenous ocrelizumab has been evaluated in 1311 patients across the MS clinical studies, which included 825 patients in active-controlled clinical trials in patients with RMS and 486 patients in a placebo-controlled study in patients with PPMS.

RMS

In active-controlled intravenous ocrelizumab clinical trials (Study 1 and Study 2), 825 patients with RMS received ocrelizumab 600 mg intravenously every 24 weeks (initial treatment was given as two separate 300 mg infusions at Weeks 0 and 2) [see Clinical Studies (14.1)]. The overall exposure in the 96-week controlled treatment periods was 1448 patient-years.

The most common adverse reactions in RMS trials (incidence ≥ 10%) were upper respiratory tract infections and infusion reactions. Table 1 summarizes the adverse reactions that occurred in active-controlled intravenous ocrelizumab RMS trials (Study 1 and Study 2).

Table 1 Adverse Reactions in Adult Patients With RMS With an Incidence of at least 5% for Intravenous Ocrelizumab and Higher than REBIF
Adverse Reactions | Studies 1 and 2
Adverse Reactions | Ocrelizumab 600 mg IV Every 24 Weeks [The first dose was given as two separate 300 mg infusions at Weeks 0 and 2.] (n=825) % | REBIF 44 mcg SQ 3 Times per Week (n=826) %
Upper respiratory tract infections | 40 | 33
Infusion reactions | 34 | 10
Depression | 8 | 7
Lower respiratory tract infections | 8 | 5
Back pain | 6 | 5
Herpes virus- associated infections | 6 | 4
Pain in extremity | 5 | 4

PPMS

In a placebo-controlled intravenous ocrelizumab clinical trial (Study 3), a total of 486 patients with PPMS received one course of ocrelizumab (600 mg of ocrelizumab administered as two 300 mg infusions two weeks apart) given intravenously every 24 weeks and 239 patients received placebo intravenously [see Clinical Studies (14.2)]. The overall exposure in the controlled treatment period was 1416 patient-years, with median treatment duration of 3 years.

The most common adverse reactions in the PPMS trial (incidence ≥ 10%) were upper respiratory tract infections, infusion reactions, skin infections, and lower respiratory tract infections. Table 2 summarizes the adverse reactions that occurred in the placebo-controlled intravenous ocrelizumab PPMS trial (Study 3).

Table 2 Adverse Reactions in Adult Patients With PPMS With an Incidence of at Least 5% for Intravenous Ocrelizumab and Higher Than Placebo
Adverse Reactions | Study 3
Adverse Reactions | Ocrelizumab 600 mg IV Every 24 Weeks [One dose of intravenous ocrelizumab (600 mg administered as two 300 mg infusions two weeks apart)] | Placebo
Adverse Reactions | (n=486) % | (n=239) %
Upper respiratory tract infections | 49 | 43
Infusion reactions | 40 | 26
Skin infections | 14 | 11
Lower respiratory tract infections | 10 | 9
Cough | 7 | 3
Diarrhea | 6 | 5
Edema peripheral | 6 | 5
Herpes virus associated infections | 5 | 4

Laboratory Abnormalities

Decreased Immunoglobulins

Ocrelizumab decreased total immunoglobulins, with the greatest decline seen in IgM levels; however, a decrease in IgG levels was associated with an increased rate of serious infections.

In the active-controlled (RMS) trials (Study 1 and Study 2), the proportion of patients at baseline reporting IgG, IgA, and IgM below the lower limit of normal (LLN) in patients treated with intravenous ocrelizumab was 0.5%, 1.5%, and 0.1%, respectively. Following treatment, the proportion of patients treated with intravenous ocrelizumab reporting IgG, IgA, and IgM below the LLN at 96 weeks was 1.5%, 2.4%, and 16.5%, respectively.

In the placebo-controlled (PPMS) trial (Study 3), the proportion of patients at baseline reporting IgG, IgA, and IgM below the LLN in patients treated with intravenous ocrelizumab was 0.0%, 0.2%, and 0.2%, respectively. Following treatment, the proportion of patients treated with intravenous ocrelizumab reporting IgG, IgA, and IgM below the LLN at 120 weeks was 1.1%, 0.5%, and 15.5%, respectively.

The pooled data of intravenous ocrelizumab clinical studies (RMS and PPMS) and their open-label extensions (up to approximately 7 years of exposure) have shown an association between decreased levels of IgG and increased rates of serious infections. The type, severity, latency, duration, and outcome of serious infections observed during episodes of immunoglobulins below LLN were consistent with the overall serious infections observed in patients treated with intravenous ocrelizumab.

Decreased Neutrophil Levels

In the PPMS clinical trial (Study 3), decreased neutrophil counts occurred in 13% of patients treated with intravenous ocrelizumab compared to 10% in placebo patients. The majority of the decreased neutrophil counts were only observed once for a given patient treated with intravenous ocrelizumab and were between the LLN and 1.0 × 10^9/L. Overall, 1% of the patients in the intravenous ocrelizumab group had neutrophil counts less than 1.0 × 10^9/L and these were not associated with an infection.

Adverse Reactions With OCREVUS ZUNOVO in Patients With RMS and PPMS

The safety of OCREVUS ZUNOVO was evaluated in Study 4, an active-controlled, open-label, randomized study in ocrelizumab-naïve patients with RMS or PPMS [see Clinical Studies (14.3)]. One hundred eighteen patients received OCREVUS ZUNOVO as their first dose and 118 patients received intravenous ocrelizumab for their first dose (two separate 300 mg infusions at Weeks 0 and 2).

The most common adverse reactions (reported in at least 10% of OCREVUS ZUNOVO-treated patients) were injection reactions.

In Study 4, injection reactions occurred in 49% (58/118) of patients after the first injection of OCREVUS ZUNOVO. Of these 118 patients, 47% and 11% experienced at least one local injection reaction and one systemic injection reaction, respectively. The most common symptoms reported by patients with local and systemic injection reactions included: injection site erythema, injection site pain, injection site swelling, injection site pruritus, headache, and nausea. Among the patients experiencing an injection reaction, the majority of patients (83%) had injection reactions occur within 24 hours after the end of the injection, as opposed to during the injection (19%). All injection reactions were of mild (73%) or moderate (27%) severity. The median duration of symptoms was 3 days for systemic injection reactions and 3.5 days for local injection reactions. All patients recovered from injection reactions, of which 26% required symptomatic treatment.

For subsequent injections, among the 118 patients who received OCREVUS ZUNOVO only throughout the study, the frequency of local injection reactions ranged from 31% to 43% and the frequency of systemic injection reactions ranged from 3% to 7% from Injection 2 to Injection 4. All injection reactions were of mild or moderate severity.

6.2 Postmarketing Experience

The following adverse reactions have been identified during postapproval use of ocrelizumab. Because these reactions are reported voluntarily from a population of uncertain size, it is not always possible to reliably estimate their frequency or establish a causal relationship to drug exposure.

Gastrointestinal Disorders: Immune-mediated colitis [see Warnings and Precautions (5.6)]

Hepatobiliary Disorders: Liver injury [see Warnings and Precautions (5.7)]

Infections and Infestations: Serious herpes infections [see Warnings and Precautions (5.2)], progressive multifocal leukoencephalopathy [see Warnings and Precautions (5.3)], and babesiosis

Skin: Pyoderma gangrenosum

7 DRUG INTERACTIONS

7.1 Immunosuppressive or Immune-Modulating Therapies

The concomitant use of OCREVUS ZUNOVO and other immune-modulating or immunosuppressive therapies, including immunosuppressant doses of corticosteroids, is expected to increase the risk of immunosuppression. Consider the risk of additive immune system effects when coadministering immunosuppressive therapies with OCREVUS ZUNOVO. When switching from drugs with prolonged immune effects, such as daclizumab, fingolimod, natalizumab, teriflunomide, or mitoxantrone, consider the duration and mode of action of these drugs because of additive immunosuppressive effects when initiating OCREVUS ZUNOVO [see Warnings and Precautions (5.2)].

7.2 Vaccinations

A Phase 3b randomized, open-label study examined the concomitant use of intravenous ocrelizumab and several non-live vaccines in adults 18-55 years of age with relapsing forms of MS (68 subjects undergoing treatment with intravenous ocrelizumab at the time of vaccination and 34 subjects not undergoing treatment with intravenous ocrelizumab at the time of vaccination). Concomitant exposure to intravenous ocrelizumab attenuated antibody responses to tetanus toxoid-containing vaccine, pneumococcal polysaccharide, pneumococcal conjugate vaccines, and seasonal inactivated influenza vaccines. The impact of the observed attenuation on vaccine effectiveness in this patient population is unknown. The safety and effectiveness of live or live-attenuated vaccines administered concomitantly with ocrelizumab have not been assessed [see Warnings and Precautions (5.2)].

8 USE IN SPECIFIC POPULATIONS

8.1 Pregnancy

Risk Summary

OCREVUS ZUNOVO is a humanized monoclonal antibody of an immunoglobulin G1 subtype and immunoglobulins are known to cross the placental barrier. There are no adequate data on the developmental risk associated with use of OCREVUS ZUNOVO or ocrelizumab-containing products in pregnant women. However, transient peripheral B-cell depletion and lymphocytopenia have been reported in infants born to mothers exposed to other anti-CD20 antibodies during pregnancy. B-cell levels in infants following maternal exposure to OCREVUS ZUNOVO or ocrelizumab-containing products have not been studied in clinical trials. The potential duration of B-cell depletion in such infants, and the impact of B-cell depletion on vaccine safety and effectiveness, is unknown [see Warnings and Precautions (5.2)].

Following administration of ocrelizumab to pregnant monkeys at doses similar to or greater than those used clinically, increased perinatal mortality, depletion of B-cell populations, and renal, bone marrow, and testicular toxicity were observed in the offspring in the absence of maternal toxicity [see Data].

In the U.S. general population, the estimated background risk of major birth defects and miscarriage in clinically recognized pregnancies is 2% to 4% and 15% to 20%, respectively. The background risk of major birth defects and miscarriage for the indicated population is unknown.

Data

Animal Data

OCREVUS ZUNOVO for subcutaneous injection contains ocrelizumab and hyaluronidase [see Description (11)].

Ocrelizumab:

- Following intravenous administration of ocrelizumab to monkeys during organogenesis (loading doses of 15 or 75 mg/kg on gestation days 20, 21, and 22, followed by weekly doses of 20 or 100 mg/kg), depletion of B-lymphocytes in lymphoid tissue (spleen and lymph nodes) was observed in fetuses at both doses.
- Intravenous administration of ocrelizumab (three daily loading doses of 15 or 75 mg/kg, followed by weekly doses of 20 or 100 mg/kg) to pregnant monkeys throughout the period of organogenesis and continuing through the neonatal period resulted in perinatal deaths (some associated with bacterial infections), renal toxicity (glomerulopathy and inflammation), lymphoid follicle formation in the bone marrow, and severe decreases in circulating B-lymphocytes in neonates. The cause of the neonatal deaths is uncertain; however, both affected neonates were found to have bacterial infections. Reduced testicular weight was observed in neonates at the high dose.
- A no-effect dose for adverse developmental effects was not identified; the doses tested in monkey are 2 and 10 times the recommended human dose of 600 mg intravenous ocrelizumab, on a mg/kg basis.

Hyaluronidase:

- In an embryo-fetal study, mice were dosed daily by subcutaneous injection during the period of organogenesis with hyaluronidase (human recombinant) at dose levels up to 2,200,000 U/kg, which is > 5,700 times higher than the human dose. The study found no evidence of teratogenicity. Reduced fetal weight and increased numbers of fetal resorptions were observed, with no effects found at a daily dose of 360,000 U/kg, which is > 940 times higher than the human dose.
- In a pre-and postnatal development study, mice have been dosed daily by subcutaneous injection, with hyaluronidase (human recombinant) from implantation through lactation and weaning at dose levels up to 1,100,000 U/kg, which is > 2,800 times higher than the human dose. The study found no adverse effects on sexual maturation, learning and memory, or fertility of the offspring.

8.2 Lactation

Risk Summary

There are no data on the presence of ocrelizumab or hyaluronidase, from administration of OCREVUS ZUNOVO, in human milk, the effects on the breastfed infant, or the effects of the drug on milk production. Ocrelizumab was excreted in the milk of ocrelizumab-treated monkeys. Human IgG is excreted in human milk, and the potential for absorption of ocrelizumab to lead to B-cell depletion in the infant is unknown. The developmental and health benefits of breastfeeding should be considered along with the mother's clinical need for OCREVUS ZUNOVO and any potential adverse effects on the breastfed infant from OCREVUS ZUNOVO or from the underlying maternal condition.

8.3 Females and Males of Reproductive Potential

Contraception

Women of childbearing potential should use effective contraception while receiving OCREVUS ZUNOVO and for 6 months after the last dose of OCREVUS ZUNOVO [see Clinical Pharmacology (12.3)].

8.4 Pediatric Use

Safety and effectiveness of OCREVUS ZUNOVO in pediatric patients have not been established.

8.5 Geriatric Use

Clinical studies of OCREVUS ZUNOVO did not include sufficient numbers of subjects aged 65 and over to determine whether they respond differently from younger subjects.

11 DESCRIPTION

Ocrelizumab is a recombinant humanized monoclonal antibody directed against CD20-expressing B-cells. Ocrelizumab is a glycosylated immunoglobulin G1 (IgG1) with a molecular mass of approximately 145 kDa.

Hyaluronidase (human recombinant) is an endoglycosidase used to increase the dispersion and absorption of co-administered drugs when administered subcutaneously. It is a glycosylated single-chain protein produced by mammalian (Chinese Hamster Ovary) cells containing a DNA plasmid encoding for a soluble fragment of human hyaluronidase (PH20). Hyaluronidase (human recombinant) has a molecular weight of approximately 61 kDa.

OCREVUS ZUNOVO (ocrelizumab and hyaluronidase-ocsq) injection for subcutaneous use is a sterile, preservative-free, clear to slightly opalescent, and colorless to pale brown solution supplied in single-dose vials. Each 23 mL of solution contains 920 mg ocrelizumab, 23,000 units of hyaluronidase (human recombinant), glacial acetic acid (5.5 mg), methionine (34.3 mg), polysorbate 20 (13.8 mg), sodium acetate (30.2 mg), trehalose (1889.5 mg), and water for injection at pH 5.3.

12 CLINICAL PHARMACOLOGY

12.1 Mechanism of Action

The precise mechanism by which ocrelizumab exerts its therapeutic effects in multiple sclerosis is unknown, but is presumed to involve binding to CD20, a cell surface antigen present on pre-B and mature B lymphocytes. Following cell surface binding to B lymphocytes, ocrelizumab results in antibody-dependent cellular cytolysis and complement-mediated lysis.

Hyaluronan is a polysaccharide found in the extracellular matrix of the subcutaneous tissue. It is depolymerized by the naturally occurring enzyme hyaluronidase. Unlike the stable structural components of the interstitial matrix, hyaluronan has a half-life of approximately 0.5 days. Hyaluronidase increases permeability of the subcutaneous tissue by depolymerizing hyaluronan. In the doses administered, hyaluronidase in OCREVUS ZUNOVO acts transiently and locally. The effects of hyaluronidase are reversible and permeability of the subcutaneous tissue is restored within 24 to 48 hours.

12.2 Pharmacodynamics

For B-cell counts, assays for CD19^+ B-cells are used because the presence of ocrelizumab interferes with the CD20 assay. In clinical studies with OCREVUS ZUNOVO and intravenous ocrelizumab, CD19^+ B-cell counts in blood were reduced by 14 days after administration. In clinical studies with intravenous ocrelizumab, B-cell counts rose to above the lower limit of normal (LLN) or above baseline counts between infusions of ocrelizumab at least one time in 0.3% to 4.1% of patients. In a clinical study of 51 patients treated with intravenous ocrelizumab, the median time for B-cell counts to return to either baseline or LLN was 72 weeks (range 27-175 weeks) after the last ocrelizumab infusion. Within 2.5 years after the last infusion, B-cell counts rose to either baseline or LLN in 90% of patients.

12.3 Pharmacokinetics

After subcutaneous administration of 920 mg ocrelizumab, the estimated mean exposure (AUC over the 24-week dosing interval) was 3730 µg/mL∙day. The mean Cmax was 132 µg/mL and tmax was reached after approximately 4 days (range 2 – 13 days). The estimated absolute bioavailability following subcutaneous administration was 81%.

In Study 4, the differences in pharmacokinetic exposures following the administration of OCREVUS ZUNOVO subcutaneously at 920 mg/23,000 units and ocrelizumab intravenously at 600 mg in MS patients were not clinically significant.

Pharmacokinetics (PK) of ocrelizumab in MS clinical studies fit a two-compartment model with time-dependent clearance.

Distribution

The population PK estimate of the central volume of distribution was 2.78 L. Peripheral volume and inter-compartment clearance were estimated at 2.68 L and 0.55 L/day, respectively.

Elimination

Constant clearance was estimated at 0.17 L/day, and initial time-dependent clearance at 0.05 L/day, which declined with a half-life of 33 weeks. The terminal elimination half-life was 20 days.

Metabolism

The metabolism of OCREVUS ZUNOVO has not been directly studied because antibodies are cleared principally by catabolism.

Specific Populations

Renal Impairment

Patients with mild renal impairment were included in clinical trials. No significant change in the pharmacokinetics of ocrelizumab was observed in those patients.

Hepatic Impairment

Patients with mild hepatic impairment were included in clinical trials. No significant change in the pharmacokinetics of ocrelizumab was observed in those patients.

12.6 Immunogenicity

As with all therapeutic proteins, there is potential for immunogenicity. Immunogenicity data are highly dependent on the sensitivity and specificity of the test methods used. Additionally, the observed incidence of a positive result in a test method may be influenced by several factors, including sample handling, timing of sample collection, drug interference, concomitant medication, and the underlying disease. Therefore, comparison of the incidence of antibodies to OCREVUS ZUNOVO with the incidence of antibodies to other products may be misleading.

In Study 4, no patients tested positive for ocrelizumab anti-drug antibodies (ADAs) or anti-rHuPH20 (hyaluronidase [human recombinant]) antibodies.

13 NONCLINICAL TOXICOLOGY

13.1 Carcinogenesis, Mutagenesis, Impairment of Fertility

OCREVUS ZUNOVO contains ocrelizumab and hyaluronidase.

No carcinogenicity studies have been performed to assess the carcinogenic potential of ocrelizumab.

No studies have been performed to assess the mutagenic potential of ocrelizumab. As an antibody, ocrelizumab is not expected to interact directly with DNA.

No effects on reproductive organs were observed in male monkeys administered ocrelizumab by intravenous injection (three loading doses of 15 or 75 mg/kg, followed by weekly doses of 20 or 100 mg/kg) for 8 weeks. There were also no effects on estrus cycle in female monkeys administered ocrelizumab over three menstrual cycles using the same dosing regimen. The doses tested in monkey are 2 and 10 times the recommended human dose of 600 mg intravenous ocrelizumab, on a mg/kg basis.

Hyaluronidases are found in most tissues of the body. Long-term animal studies have not been performed to assess the carcinogenic or mutagenic potential of hyaluronidase. In addition, when subcutaneous hyaluronidase (recombinant human) was administered to cynomolgus monkeys for 39 weeks at dose levels up to 220,000 U/kg, which is > 570 times higher than the human dose, no evidence of toxicity to the male or female reproductive system was found through periodic monitoring of in-life parameters, e.g., semen analyses, hormone levels, menstrual cycles, and also from gross pathology, histopathology and organ weight data.

14 CLINICAL STUDIES

Studies 1-3 (described below), which established the effectiveness of ocrelizumab for the treatment of RMS and PPMS in adults, were conducted with intravenously-administered ocrelizumab. Study 4 demonstrated comparable exposure of OCREVUS ZUNOVO relative to the ocrelizumab intravenous formulation, which established the efficacy of OCREVUS ZUNOVO [see Clinical Pharmacology (12.3)].

14.1 Intravenous Ocrelizumab in Patients With Relapsing Forms of Multiple Sclerosis

The efficacy of intravenous ocrelizumab was demonstrated in two randomized, double-blind, double-dummy, active comparator-controlled clinical trials of identical design, in patients with relapsing forms of multiple sclerosis (RMS) treated for 96 weeks (Study 1; NCT01247324 and Study 2; NCT01412333). The dose of intravenous ocrelizumab was 600 mg every 24 weeks (initial treatment was given as two 300 mg IV infusions administered 2 weeks apart, and subsequent doses were administered as a single 600 mg IV infusion) and placebo subcutaneous injections were given 3 times per week. The dose of REBIF, the active comparator, was 44 mcg given as subcutaneous injections 3 times per week and placebo IV infusions were given every 24 weeks. Both studies included patients who had experienced at least one relapse within the prior year, or two relapses within the prior two years, and had an Expanded Disability Status Scale (EDSS) score from 0 to 5.5. Patients with primary progressive forms of multiple sclerosis (MS) were excluded. Neurological evaluations were performed every 12 weeks and at the time of a suspected relapse. Brain MRIs were performed at baseline and at Weeks 24, 48, and 96.

The primary outcome of both Study 1 and Study 2 was the annualized relapse rate (ARR). Additional outcome measures included the proportion of patients with confirmed disability progression, the mean number of MRI T1 gadolinium (Gd)-enhancing lesions at Weeks 24, 48, and 96, and new or enlarging MRI T2 hyperintense lesions. Progression of disability was defined as an increase of 1 point or more from the baseline EDSS score attributable to MS when the baseline EDSS score was 5.5 or less, or 0.5 points or more when the baseline EDSS score was above 5.5. Disability progression was considered confirmed when the increase in the EDSS was confirmed at a regularly scheduled visit 12 weeks after the initial documentation of neurological worsening. The primary population for analysis of confirmed disability progression was the pooled population from Studies 1 and 2.

In Study 1, 410 patients were randomized to intravenous ocrelizumab and 411 to REBIF; 11% of intravenous ocrelizumab-treated patients and 17% of REBIF-treated patients did not complete the 96-week double-blind treatment period. The baseline demographic and disease characteristics were balanced between the two treatment groups. At baseline, the mean age of patients was 37 years; 66% were female. The mean time from MS diagnosis to randomization was 3.8 years, the mean number of relapses in the previous year was 1.3, and the mean EDSS score was 2.8; 74% of patients had not been treated with a non-steroid therapy for MS in the 2 years prior to the study. At baseline, 40% of patients had one or more T1 Gd-enhancing lesions (mean 1.8).

In Study 2, 417 patients were randomized to intravenous ocrelizumab and 418 to REBIF; 14% of intravenous ocrelizumab-treated patients and 23% of REBIF-treated patients did not complete the 96-week double-blind treatment period. The baseline demographic and disease characteristics were balanced between the two treatment groups. At baseline, the mean age of patients was 37 years; 66% were female. The mean time from MS diagnosis to randomization was 4.1 years, the mean number of relapses in the previous year was 1.3, and the mean EDSS score was 2.8; 74% of patients had not been treated with a non-steroid therapy for MS in the 2 years prior to the study. At baseline, 40% of intravenous ocrelizumab-treated patients had one or more T1 Gd-enhancing lesions (mean 1.9).

In Study 1 and Study 2, intravenous ocrelizumab significantly lowered the annualized relapse rate and the proportion of patients with disability progression confirmed at 12 weeks after onset compared to REBIF. Results for Study 1 and Study 2 are presented in Table 3 and Figure 1.

Table 3 Key Clinical and MRI Endpoints in RMS Patients From Study 1 and Study 2
Endpoints | Study 1 |  | Study 2
Endpoints | Intravenous Ocrelizumab 600 mg | REBIF 44 mcg three times a week | Intravenous Ocrelizumab 600 mg | REBIF 44 mcg three times a week
Endpoints | every 24 weeks N=410 | N=411 | every 24 weeks N=417 | N=418
Clinical Endpoints
Annualized Relapse Rate (Primary Endpoint) | 0.156 | 0.292 | 0.155 | 0.290
Relative Reduction | 46% (p<0.0001) |  | 47% (p<0.0001)
Proportion Relapse-free | 83% | 71% | 82% | 72%
Proportion of Patients with 12-week Confirmed Disability Progression [Defined as an increase of 1.0 point or more from the baseline Expanded Disability Status Scale (EDSS) score for patients with baseline score of 5.5 or less, or 0.5 or more when the baseline score is greater than 5.5, Kaplan-Meier estimates at Week 96.] | 9.8% Intravenous Ocrelizumab vs 15.2% REBIF
Risk Reduction (Pooled Analysis [Data prospectively pooled from Study 1 and Study 2.]) | 40%; p=0.0006
MRI Endpoints
Mean number of T1 Gd-enhancing lesions per MRI scan | 0.016 | 0.286 | 0.021 | 0.416
Relative Reduction | 94% (p<0.0001) |  | 95% (p<0.0001)
Mean number of new and/or enlarging T2 hyperintense lesions per MRI | 0.323 | 1.413 | 0.325 | 1.904
Relative Reduction | 77% (p<0.0001) |  | 83% (p<0.0001)

Figure 1 Kaplan-Meier Plot [Pre-specified pooled analysis of Study 1 and 2] of Time to Onset of Confirmed Disability Progression Sustained for at Least 12 Weeks With the Initial Event of Neurological Worsening Occurring During the Double-Blind Treatment Period in Pooled Studies 1 and 2 in Patients With RMS (Pooled ITT Population)

In exploratory subgroup analyses of Study 1 and Study 2, the effect of intravenous ocrelizumab on annualized relapse rate and disability progression was similar in male and female patients.

14.2 Intravenous Ocrelizumab in Patients With Primary Progressive Multiple Sclerosis

Study 3 was a randomized, double-blind, placebo-controlled clinical trial in patients with primary progressive multiple sclerosis (PPMS) (NCT01194570). Patients were randomized 2:1 to receive either intravenous ocrelizumab 600 mg or placebo as two 300 mg intravenous infusions 2 weeks apart every 24 weeks for at least 120 weeks. Selection criteria required a baseline EDSS of 3 to 6.5 and a score of 2 or greater for the EDSS pyramidal functional system due to lower extremity findings. Neurological assessments were conducted every 12 weeks. An MRI scan was obtained at baseline and at Weeks 24, 48, and 120.

In Study 3, the primary outcome was the time to onset of disability progression attributable to MS confirmed to be present at the next neurological assessment at least 12 weeks later. Disability progression occurred when the EDSS score increased by 1 point or more from the baseline EDSS if the baseline EDSS was 5.5 points or less, or by 0.5 points or more if the baseline EDSS was more than 5.5 points. In Study 3, confirmed disability progression also was deemed to have occurred if patients who had onset of disability progression discontinued participation in the study before the next assessment. Additional outcome measures included timed 25-foot walk, and percentage change in T2 hyperintense lesion volume.

Study 3 randomized 488 patients to intravenous ocrelizumab and 244 to placebo; 21% of intravenous ocrelizumab-treated patients and 34% of placebo-treated patients did not complete the trial. The baseline demographic and disease characteristics were balanced between the two treatment groups. At baseline, the mean age of patients was 45; 49% were female. The mean time since symptom onset was 6.7 years, the mean EDSS score was 4.7, and 26% had one or more T1 Gd-enhancing lesions at baseline; 88% of patients had not been treated previously with a non-steroid treatment for MS. The time to onset of disability progression confirmed at 12 weeks after onset was significantly longer for intravenous ocrelizumab-treated patients than for placebo-treated patients (see Figure 2). Results for Study 3 are presented in Table 4 and Figure 2.

Table 4 Key Clinical and MRI Endpoints in PPMS Patients for Study 3
Endpoints | Study 3
Endpoints | Intravenous Ocrelizumab 600 mg (two 300 mg infusions two weeks apart every 24 weeks) | Placebo
Endpoints | N=488 | N=244
Clinical Outcomes
Proportion of patients with 12-week Confirmed Disability Progression [Defined as an increase of 1.0 point or more from the baseline EDSS score for patients with baseline score of 5.5 or less, or an increase of 0.5 or more when the baseline score is more than 5.5.] | 32.9% | 39.3%
Risk reduction | 24%; p=0.0321
MRI Endpoints
Mean change in volume of T2 lesions, from baseline to Week 120 (cm^3) | -0.39 | 0.79
Mean change in volume of T2 lesions, from baseline to Week 120 (cm^3) | p<0.0001

Figure 2 Kaplan-Meier Plot of Time to Onset of Confirmed Disability Progression Sustained for at Least 12 Weeks With the Initial Event of Neurological Worsening Occurring During the Double-Blind Treatment Period in Study 3 [All patients in this analysis had a minimum of 120 weeks of follow-up. The primary analysis is based on all disability progression events accrued including 21 without confirmatory EDSS at 12 weeks.]

In the overall population in Study 3, the proportion of patients with 20 percent worsening of the timed 25-foot walk confirmed at 12 weeks was 49% in intravenous ocrelizumab-treated patients compared to 59% in placebo-treated patients (25% risk reduction).

In exploratory subgroup analyses of Study 3, the proportion of female patients with disability progression confirmed at 12 weeks after onset was similar in intravenous ocrelizumab-treated patients and placebo-treated patients (approximately 36% in each group). In male patients, the proportion of patients with disability progression confirmed at 12 weeks after onset was approximately 30% in intravenous ocrelizumab-treated patients and 43% in placebo-treated patients. Clinical and MRI endpoints that generally favored intravenous ocrelizumab numerically in the overall population, and that showed similar trends in both male and female patients, included annualized relapse rate, change in T2 lesion volume, and number of new or enlarging T2 lesions.

14.3 OCREVUS ZUNOVO in Patients With RMS or PPMS

Study 4 was a multicenter, randomized, open-label, parallel arm trial conducted to evaluate the comparative bioavailability, pharmacokinetics, pharmacodynamics, safety, and immunogenicity of OCREVUS ZUNOVO compared with intravenous ocrelizumab in patients with either RMS or PPMS (NCT05232825).

Study 4 enrolled 236 patients (213 with RMS, 23 with PPMS), 18-65 years of age with an EDSS between 0 to 6.5 at screening. The demographics were similar and baseline characteristics were balanced across the two treatment groups. The mean age was 40 years in both groups. In the OCREVUS ZUNOVO group, 35% of patients were male and the mean/median duration since MS diagnosis was 5.7/3.1 years, compared to 41% male and 4.8/2.4 years in the ocrelizumab IV group.

16 HOW SUPPLIED/STORAGE AND HANDLING

OCREVUS ZUNOVO (ocrelizumab and hyaluronidase-ocsq) injection for subcutaneous use is a sterile, preservative-free, clear to slightly opalescent, and colorless to pale brown solution supplied as a carton containing one 920 mg and 23,000 units/23 mL (40 mg and 1,000 units/mL) single-dose vial (NDC 50242-554-01).

STORAGE AND HANDLING

Store OCREVUS ZUNOVO vials refrigerated at 2°C to 8°C (36°F to 46°F) in the original carton to protect from light. Do not freeze or shake.

If necessary, OCREVUS ZUNOVO can be removed and placed back into the refrigerator. Unopened OCREVUS ZUNOVO vials may be stored in the original carton for a cumulative time of up to 12 hours without refrigeration at a temperature up to 25°C (77°F).

17 PATIENT COUNSELING INFORMATION

Advise the patient to read the FDA-approved patient labeling (Medication Guide).

Injection Reactions

Inform patients that the signs and symptoms of injection reactions can be local or systemic, and that injection reactions can occur up to 24 hours after injection. Advise patients to contact their healthcare provider immediately for signs or symptoms of injection reactions [see Warnings and Precautions (5.1)].

Infection

Advise patients to contact their healthcare provider for any signs of infection during treatment or after the last dose [see Clinical Pharmacology (12.2)]. Signs include fever, chills, constant cough, dysuria, or signs of herpes such as cold sores, shingles, or genital sores [see Warnings and Precautions (5.2)].

Advise patients that OCREVUS ZUNOVO may cause reactivation of hepatitis B infection and that monitoring will be required if they are at risk [see Warnings and Precautions (5.2)].

Advise patients that herpes infections, including serious herpes infections affecting the central nervous system, skin, and eyes, have occurred during treatment with ocrelizumab. Advise patients to promptly contact their healthcare provider if they experience any signs or symptoms of herpes infections including oral or genital symptoms, fever, skin rash, pain, itching, decreased visual acuity, eye redness, eye pain, headache, neck stiffness, or change in mental status [see Warnings and Precautions (5.2)].

Vaccination

Advise patients to complete any required live or live-attenuated vaccinations at least 4 weeks and, whenever possible, non-live vaccinations at least 2 weeks prior to initiation of ocrelizumab treatment. Administration of live-attenuated or live vaccines is not recommended during OCREVUS ZUNOVO treatment and until B-cell recovery [see Warnings and Precautions (5.2)].

Progressive Multifocal Leukoencephalopathy

Inform patients that PML has occurred in patients who received ocrelizumab, and may happen with OCREVUS ZUNOVO. Inform the patient that PML is characterized by a progression of deficits and usually leads to death or severe disability over weeks or months. Instruct the patient of the importance of contacting their healthcare provider if they develop any symptoms suggestive of PML. Inform the patient that typical symptoms associated with PML are diverse, progress over days to weeks, and include progressive weakness on one side of the body or clumsiness of limbs, disturbance of vision, and changes in thinking, memory, and orientation leading to confusion and personality changes [see Warnings and Precautions (5.3)].

Malignancies

Advise patients that an increased risk of malignancy, including breast cancer, may exist with OCREVUS ZUNOVO. Advise patients that they should follow standard breast cancer screening guidelines [see Warnings and Precautions (5.5)].

Immune-Mediated Colitis

Advise patients to promptly contact their healthcare provider if they experience any signs and symptoms of colitis, including diarrhea, abdominal pain, and blood in stool [see Warnings and Precautions (5.6)].

Liver Injury

Inform patients that liver injury has been reported with anti-CD20 B-cell depleting therapies, including ocrelizumab. Instruct patients treated with OCREVUS ZUNOVO to promptly report any symptoms that may indicate liver injury, including fatigue, anorexia, nausea, vomiting, right upper abdominal discomfort, dark urine, or jaundice. A blood test should be obtained before patients start therapy, and during treatment as clinically indicated [see Warnings and Precautions (5.7)].

Contraception

Females of childbearing potential should use effective contraception while receiving OCREVUS ZUNOVO and for 6 months after the last injection of OCREVUS ZUNOVO [see Clinical Pharmacology (12.3)]. Instruct patients that if they are pregnant or plan to become pregnant while taking OCREVUS ZUNOVO, they should inform their healthcare provider [see Use in Specific Populations (8.1)].

OCREVUS ZUNOVO® [ocrelizumab and hyaluronidase-ocsq]

Manufactured by:
Genentech, Inc.
A Member of the Roche Group
1 DNA Way
South San Francisco, CA 94080-4990

U.S. License No. 1048

OCREVUS ZUNOVO is a registered trademark of Genentech, Inc.
©2025 Genentech, Inc.

MEDICATION GUIDE
OCREVUS ZUNOVO® (OH-creh-vus zoo-NOH-voh)
(ocrelizumab and hyaluronidase-ocsq)
injection, for subcutaneous use

What is the most important information I should know about OCREVUS ZUNOVO?
OCREVUS ZUNOVO can cause serious side effects, including:

- Injection reactions: Injection reactions are a common side effect of OCREVUS ZUNOVO, which can be serious and may require you to be hospitalized. You will be monitored for signs and symptoms of an injection reaction when you receive OCREVUS ZUNOVO. This will happen during all injections, for at least 1 hour after your first injection, and for at least 15 minutes after all injections following the first injection. Tell your healthcare provider or nurse if you get any of these symptoms:

- itchy skin
- rash
- hives
- tiredness
- coughing or wheezing

- trouble breathing
- throat irritation or pain
- feeling faint
- fever
- redness on your face (flushing)

- nausea
- headache
- swelling of the throat
- dizziness
- injection site pain, swelling or redness

- shortness of breath
- fatigue
- fast heart beat

These injection reactions can happen during or up to 24 hours after your injection. It is important that you call your healthcare provider right away if you get any of the signs or symptoms listed above after each injection.

- Infection:

- Infections are a common side effect. OCREVUS ZUNOVO increases your risk of getting upper respiratory tract infections, lower respiratory tract infections, skin infections, and herpes infections. Serious infections can happen with OCREVUS ZUNOVO, which can be life-threatening or cause death. Tell your healthcare provider if you have an infection or have any of the following signs of infection including fever, chills, or a cough that does not go away, or painful urination. Signs of herpes infection include:

- cold sores
- shingles

- genital sores
- skin rash

- pain
- itching

Signs of a more serious herpes infection include:

- changes in vision
- eye redness or eye pain

- severe or persistent headache
- stiff neck

- confusion

Signs of infection can happen during treatment or after you have received your last dose of OCREVUS ZUNOVO. Tell your healthcare provider right away if you have an infection. Your healthcare provider should delay your treatment with OCREVUS ZUNOVO until your infection is gone.

- Hepatitis B virus (HBV) reactivation: Before starting treatment with ocrelizumab, your healthcare provider will do blood tests to check for hepatitis B viral infection. If you have ever had hepatitis B virus infection, the hepatitis B virus may become active again during or after treatment with OCREVUS ZUNOVO. Hepatitis B virus becoming active again (called reactivation) may cause serious liver problems including liver failure or death. Your healthcare provider will monitor you if you are at risk for hepatitis B virus reactivation during treatment and after you stop receiving OCREVUS ZUNOVO.

- Weakened immune system: OCREVUS ZUNOVO taken before or after other medicines that weaken the immune system could increase your risk of getting infections.

- Progressive Multifocal Leukoencephalopathy (PML): PML is a rare brain infection that usually leads to death or severe disability, and has been reported with ocrelizumab. Symptoms of PML get worse over days to weeks. It is important that you call your healthcare provider right away if you have any new or worsening neurologic signs or symptoms that have lasted several days, including problems with:

- thinking
- eyesight
- strength

- balance
- weakness on 1 side of your body
- using your arms or legs

- Decreased immunoglobulins: OCREVUS ZUNOVO may cause a decrease in some types of antibodies. Your healthcare provider will do blood tests to check your blood immunoglobulin levels.

See "What are the possible side effects of OCREVUS ZUNOVO?" for more information about side effects.

What is OCREVUS ZUNOVO?
OCREVUS ZUNOVO is a prescription medicine used to treat:

- relapsing forms of multiple sclerosis (MS), to include clinically isolated syndrome, relapsing-remitting disease, and active secondary progressive disease, in adults.
- primary progressive MS, in adults.

It is not known if OCREVUS ZUNOVO is safe and effective in children.

Who should not receive OCREVUS ZUNOVO?
Do not receive OCREVUS ZUNOVO if you:

- have an active hepatitis B virus (HBV) infection.
- have had a life-threatening administration reaction to ocrelizumab.
- have had a life-threatening allergic reaction to ocrelizumab, hyaluronidase, or any of the ingredients of OCREVUS ZUNOVO. Tell your healthcare provider if you have had an allergic reaction to OCREVUS ZUNOVO or any of its ingredients in the past. See "What are the ingredients in OCREVUS ZUNOVO?" for a complete list of ingredients in OCREVUS ZUNOVO.

Before receiving OCREVUS ZUNOVO, tell your healthcare provider about all of your medical conditions, including if you:

- have or think you have an infection. See "What is the most important information I should know about OCREVUS ZUNOVO?"
- have ever taken, take, or plan to take medicines that affect your immune system, or other treatments for MS. These medicines could increase your risk of getting an infection.
- have ever had hepatitis B or are a carrier of the hepatitis B virus.
- have a history of inflammatory bowel disease or colitis.
- have a history of liver problems.
- have had a recent vaccination or are scheduled to receive any vaccinations.
  - You should receive any required 'live' or 'live-attenuated' vaccines at least 4 weeks before you start treatment with OCREVUS ZUNOVO. You should not receive 'live' or 'live-attenuated' vaccines while you are being treated with OCREVUS ZUNOVO and until your healthcare provider tells you that your immune system is no longer weakened.
  - When possible, you should receive any 'non-live' vaccines at least 2 weeks before you start treatment with OCREVUS ZUNOVO. If you would like to receive any non-live (inactivated) vaccines, including the seasonal flu vaccine, while you are being treated with OCREVUS ZUNOVO, talk to your healthcare provider.
  - If you have a baby and you received OCREVUS ZUNOVO during your pregnancy, it is important to tell your baby's healthcare provider about receiving OCREVUS ZUNOVO so they can decide when your baby should be vaccinated.
- are pregnant, think that you might be pregnant, or plan to become pregnant. It is not known if OCREVUS ZUNOVO will harm your unborn baby. You should use birth control (contraception) during treatment with OCREVUS ZUNOVO and for 6 months after your last injection of OCREVUS ZUNOVO. Talk with your healthcare provider about what birth control method is right for you during this time. Tell your healthcare provider if you become pregnant while receiving OCREVUS ZUNOVO.
- are breastfeeding or plan to breastfeed. It is not known if OCREVUS ZUNOVO passes into your breast milk. Talk to your healthcare provider about the best way to feed your baby if you take OCREVUS ZUNOVO.

Tell your healthcare provider about all the medicines you take, including prescription and over-the-counter medicines, vitamins, and herbal supplements.

How will I receive OCREVUS ZUNOVO?

- OCREVUS ZUNOVO should be administered by a healthcare professional.
- OCREVUS ZUNOVO is given through an injection (subcutaneous injection) in your stomach.
- Before treatment with OCREVUS ZUNOVO, your healthcare provider will give you a corticosteroid medicine and an antihistamine to help reduce injection reactions (make them less frequent and less severe). You may also receive other medicines to help reduce injection reactions. See "What is the most important information I should know about OCREVUS ZUNOVO?"
- Each injection will last about 10 minutes and will be given every 6 months.

What are the possible side effects of OCREVUS ZUNOVO?
OCREVUS ZUNOVO may cause serious side effects, including:

- see "What is the most important information I should know about OCREVUS ZUNOVO?"
- Risk of cancers (malignancies) including breast cancer: Follow your healthcare provider's instructions about standard screening guidelines for breast cancer.
- Inflammation of the colon, or colitis: Tell your healthcare provider if you have any symptoms of colitis, such as:
  - Diarrhea (loose stools) or more frequent bowel movements than usual
  - Stools that are black, tarry, sticky or have blood or mucus
  - Severe stomach-area (abdomen) pain or tenderness
- Liver damage: OCREVUS ZUNOVO may cause liver damage. Your healthcare provider will do blood tests to check your liver before you start OCREVUS ZUNOVO and while you take OCREVUS ZUNOVO if needed. Tell your healthcare provider right away if you have any symptoms of liver damage, such as:
  - yellowing of the skin and eyes (jaundice)
  - nausea
  - vomiting
  - unusual darkening of the urine
  - feeling tired or weak

The most common side effects of OCREVUS ZUNOVO include:

- injection reactions
- respiratory tract infections
- skin infections

These are not all the possible side effects of OCREVUS ZUNOVO.
Call your doctor for medical advice about side effects. You may report side effects to FDA at 1-800-FDA-1088.

General information about the safe and effective use of OCREVUS ZUNOVO.
Medicines are sometimes prescribed for purposes other than those listed in a Medication Guide. You can ask your pharmacist or healthcare provider for information about OCREVUS ZUNOVO that is written for health professionals.

What are the ingredients in OCREVUS ZUNOVO?
Active ingredient: ocrelizumab and hyaluronidase-ocsq.
Inactive ingredients: glacial acetic acid, methionine, polysorbate 20, sodium acetate, trehalose, and water for injection.
Manufactured by: Genentech, Inc., A Member of the Roche Group, 1 DNA Way, South San Francisco, CA 94080-4990
U.S. License No. 1048
For more information, go to www.OCREVUS.com or call 1-844-627-3887.

This Medication Guide has been approved by the U.S. Food and Drug Administration

Issued: 8/2025

PRINCIPAL DISPLAY PANEL - 23 mL Vial Carton

NDC 50242-554-01

Ocrevus Zunovo®
(ocrelizumab and
hyaluronidase-ocsq)
Injection

920 mg and
23,000 units/23 mL
(40 mg and 1,000 units/mL)

For Subcutaneous Use Only.
For subcutaneous injection in the
abdomen over approximately 10 minutes.

Single-Dose Vial.
Discard Unused Portion.

Attention Pharmacist: Dispense the
accompanying Medication Guide to
each patient.

1 vial

Rx only
Genentech

11038285